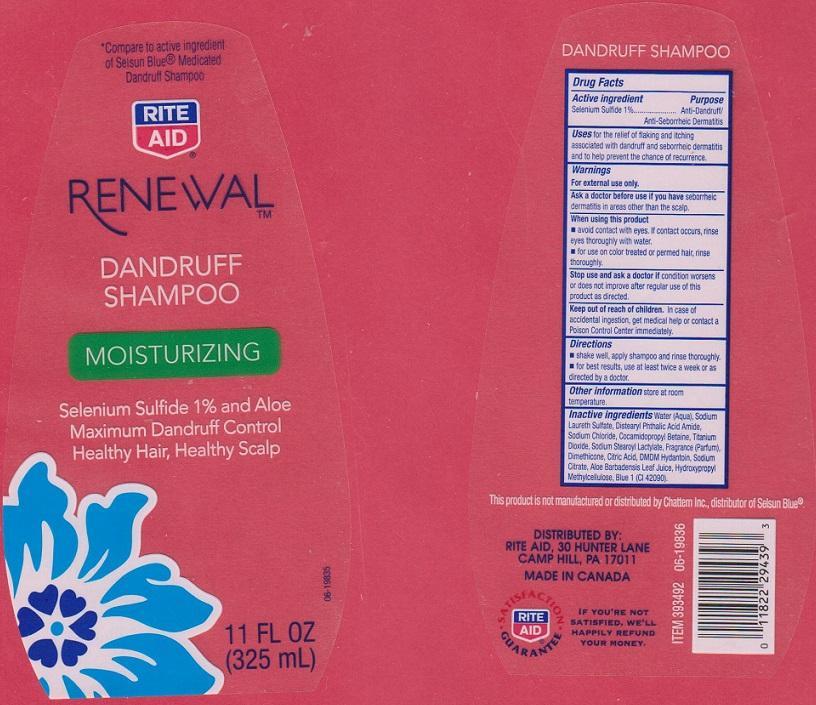 DRUG LABEL: RENEWAL
NDC: 11822-6221 | Form: LIQUID
Manufacturer: RITE AID CORPORATION
Category: otc | Type: HUMAN OTC DRUG LABEL
Date: 20150304

ACTIVE INGREDIENTS: SELENIUM SULFIDE 10 mg/1 mL
INACTIVE INGREDIENTS: WATER; SODIUM LAURETH SULFATE; DISTEARYL PHTHALAMIC ACID; SODIUM CHLORIDE; COCAMIDOPROPYL BETAINE; TITANIUM DIOXIDE; SODIUM STEAROYL LACTYLATE; DIMETHICONE; CITRIC ACID MONOHYDRATE; DMDM HYDANTOIN; SODIUM CITRATE; ALOE VERA LEAF; HYPROMELLOSES; FD&C BLUE NO. 1

DRUG FACTS

ACTIVE INGREDIENT

SELENIUM SULFIDE 1%

PURPOSE

ANTI-DANDRUFF/ANTI-SEBORRHEIC DERMATITIS

USES

FOR THE RELIEF OF FLAKING AND ITCHING ASSOCIATED WITH DANDRUFF AND SEBORRHEIC DERMATITIS AND TO HELP PREVENT THE CHANCE OF RECURRENCE

WARNINGS

FOR EXTERNAL USE ONLY

ASK A DOCTOR BEFORE USE IF YOU HAVE

SEBORRHEIC DERMATITIS IN AREAS OTHER THAN THE SCALP

WHEN USING THIS PRODUCT

- AVOID CONTACT WITH EYES. IF CONTACT OCCURS, RINSE EYES THOROUGHLY WITH WATER
- FOR USE ON COLOR TREATED OR PERMED HAIR, RINSE THOROUGHLY

STOP USE AND ASK A DOCTOR IF

CONDITION WORSENS OR DOES NOT IMPROVE AFTER REGULAR USE OF THIS PRODUCT AS DIRECTED

KEEP OUT OF REACH OF CHILDREN

IN CASE OF ACCIDENTAL INGESTION, GET MEDICAL HELP OR CONTACT A POISON CONTROL CENTER IMMEDIATELY

DIRECTIONS

- SHAKE WELL, APPLY SHAMPOO AND RINSE THOROUGHLY
- FOR BEST RESULTS, USE AT LEAST TWICE A WEEK OR AS DIRECTED BY A DOCTOR

OTHER INFORMATION

STORE AT ROOM TEMPERATURE

INACTIVE INGREDIENTS

WATER (AQUA), SODIUM LAURETH SULFATE, DISTEARYL PHTHALIC ACID AMIDE, SODIUM CHLORIDE, COCAMIDOPROPYL BETAINE, TITANIUM DIOXIDE, SODIUM STEAROYL LACTYLATE, FRAGRANCE (PARFUM), DIMETHICONE, CITRIC ACID, DMDM HYDANTOIN, SODIUM CITRATE, ALOE BARBADENSIS LEAF JUICE, HYDROXYPROPYL METHYLCELLULOSE, BLUE 1 (CI 42090)